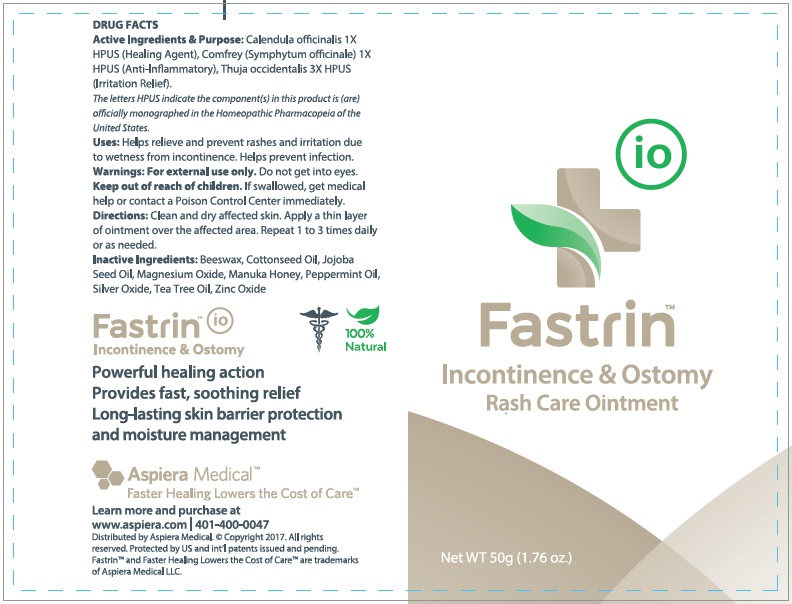 DRUG LABEL: Fastrin Incontinence and Ostomy Rash Care
NDC: 24909-603 | Form: OINTMENT
Manufacturer: Aidance Skincare & Topical Solutions, LLC
Category: homeopathic | Type: HUMAN OTC DRUG LABEL
Date: 20170601

ACTIVE INGREDIENTS: CALENDULA OFFICINALIS FLOWER 1 [hp_X]/100 g; COMFREY 1 [hp_X]/100 g; THUJA OCCIDENTALIS WHOLE 3 [hp_X]/100 g
INACTIVE INGREDIENTS: COTTONSEED OIL; HONEY; JOJOBA OIL; MAGNESIUM OXIDE; PEPPERMINT OIL; SILVER OXIDE; TEA TREE OIL; WHITE WAX; ZINC OXIDE

Drug Facts

Active Ingredient

Calendula officinalis 1X HPUS, Comfrey (Symphytum officinale) 1X HPUS, Thuja occidentalis 3X HPUS

Purpose

Calendula - Healing Agent, Comfrey - Anti-Inflammatory, Thuja - Irritation Relief

Uses

Helps relieve and prevent rashes and irritation due to wetness from incontinence. Helps prevent infection.

Warnings

For external use only. Do not get into eyes.

Keep out of reach of children.

If swallowed, get medical help or contact a Poison Control Center immediately.

Directions

Clean and dry affected skin. Apply a thin layer of ointment over the affected area. Repeat 1 to 3 times daily or as needed.

Inactive Ingredients

Beeswax, Cottonseed Oil, Jojoba Seed Oil, Magnesium Oxide, Manuka Honey, Peppermint Oil, Silver Oxide, Tea Tree Oil, Zinc Oxide

PRINCIPAL DISPLAY PANEL - 50g Tube

Fastrin

Incontinence & Ostomy

Rash Care Ointment

Net WT 50g (1.76 oz.)